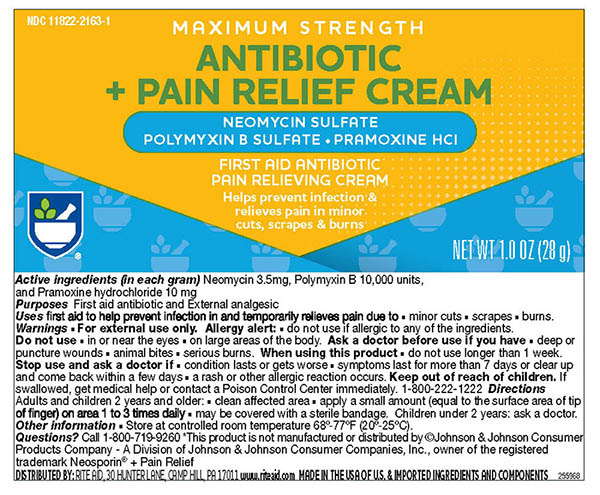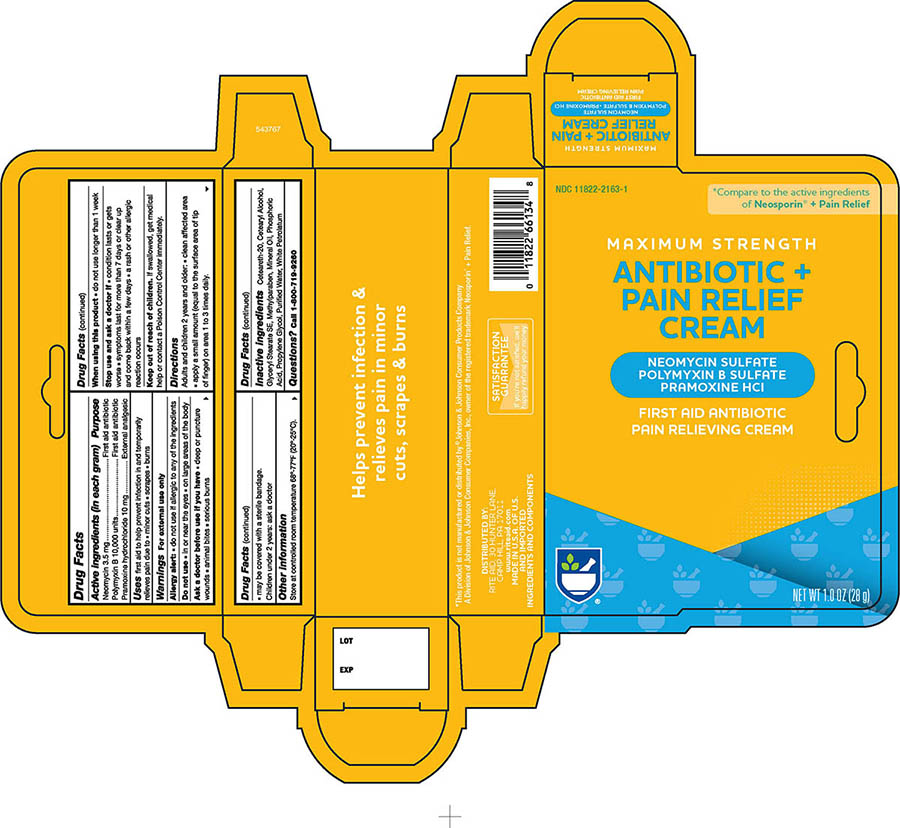 DRUG LABEL: Rite Aid Pharmacy Antibiotic With Pain Relief
NDC: 11822-2163 | Form: CREAM
Manufacturer: RITE AID
Category: otc | Type: HUMAN OTC DRUG LABEL
Date: 20241121

ACTIVE INGREDIENTS: POLYMYXIN B SULFATE 10000 [USP'U]/1 g; NEOMYCIN SULFATE 3.5 mg/1 g; PRAMOXINE HYDROCHLORIDE 10 mg/1 g
INACTIVE INGREDIENTS: POLYOXYL 20 CETOSTEARYL ETHER; CETOSTEARYL ALCOHOL; GLYCERYL STEARATE SE; METHYLPARABEN; MINERAL OIL; PHOSPHORIC ACID; PROPYLENE GLYCOL; WATER; WHITE PETROLATUM

Active ingredient

Neomycin Sulfate (3.5mg)
Polymixin B Sulfate (10,000 units)
Pramoxine Hydrochloride (10 mg)

Purpose

Neomycin Sulfate First Aid Antibiotic
Polymixin B Sulfate First Aid Antibiotic
Pramoxine Hydrochloride External Analgesic

Uses

first aid to prevent infection and for the temporary relief of pain or discomfort in minor:

cuts
scapes
burns

Warnings

For external use only.

Keep this and all drugs out of the reach of children

If swallowed, get medical help or contact Poison Control Center right away.

Directions

Adults and children 2 years of age and older:

- clean the affected area
- apply a small amount of this product (an amount equal to the surface area of the tip of a finger) on the area 1 to 3 times daily
- may be covered with a sterile bandage
- children under 2 years of age: ask a doctor

Other Information

- store at 20° to 25°C (68° to 77°F)

Inactive Ingredients

Ceteareth-20, Cetearyl Alcohol, Glyceryl Stearate SE, Methylparaben, Mineral Oil, Phosphoric Acid, Propylene Glycol, Purified Water, White Petrolatum

Principal Primary Panel -Tube

Rite Aid Multi Antibiotic Cream with Pain Relief

NDC 11822-2163-1

- Neomycin Sulfate
- Polymixin B Sulfate
- Pramoxine HCL

First aid Antibiotic Pain Relieving Cream

NET WT 1.0 OZ (28g)

Principal Primary Panel -Carton

Rite Aid Multi Antibiotic Cream with Pain Relief

NDC 11822-2163-1

- Neomycin Sulfate
- Polymixin B Sulfate
- Pramoxine HCL

First aid Antibiotic Pain Relieving Cream

NET WT 1.0 OZ (28g)